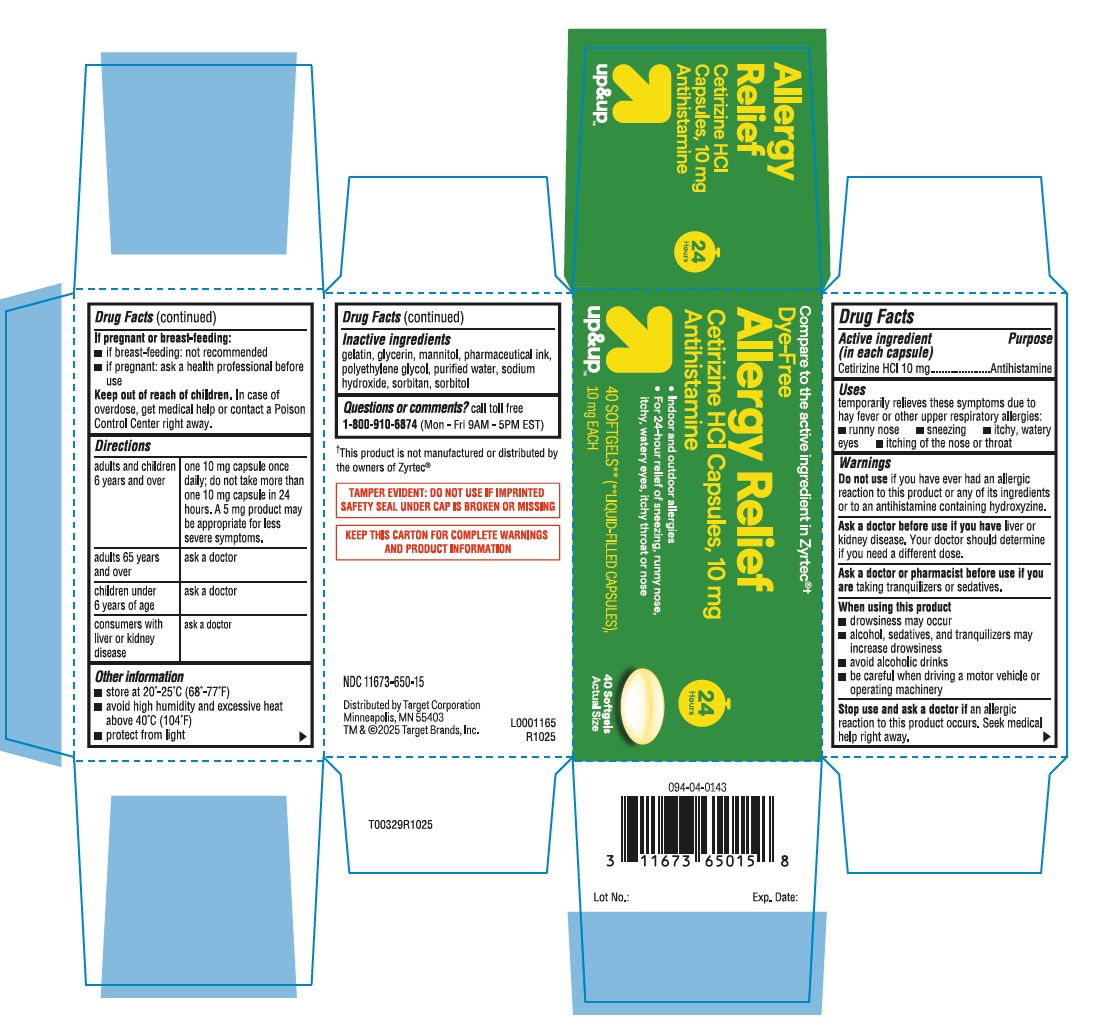 DRUG LABEL: Cetirizine HCl
NDC: 11673-650 | Form: CAPSULE
Manufacturer: TARGET Corporation
Category: otc | Type: HUMAN OTC DRUG LABEL
Date: 20251208

ACTIVE INGREDIENTS: CETIRIZINE HYDROCHLORIDE 10 mg/1 1
INACTIVE INGREDIENTS: GELATIN; GLYCERIN; MANNITOL; POLYETHYLENE GLYCOL, UNSPECIFIED; WATER; SODIUM HYDROXIDE; SORBITAN; SORBITOL

Drug Facts

Active ingredient (in each capsule)

Cetirizine HCl 10 mg

Purpose

Antihistamine

Uses

temporarily relieves these symptoms due to hay fever or other upper respiratory allergies:

- runny nose
- sneezing
- itchy, watery eyes
- itching of the nose or throat

Warnings

Do not use

if you have ever had an allergic reaction to this product or any of its ingredients or to an antihistamine containing hydroxyzine.

Ask a doctor before use if you have

liver or kidney disease. Your doctor should determine if you need a different dose.

Ask a doctor or pharmacist before use if you are

taking tranquilizers or sedatives.

When using this product

- drowsiness may occur
- alcohol, sedatives, and tranquilizers may increase drowsiness
- avoid alcoholic drinks
- be careful when driving a motor vehicle or operating machinery

Stop use and ask a doctor if

an allergic reaction to this product occurs. Seek medical help right away.

If pregnant or breast-feeding:

- if breast-feeding: not recommended
- if pregnant: ask a health professional before use

Keep out of reach of children.

In case of overdose, get medical help or contact a Poison Control Center right away.

Directions

adults and children 6 years and over | one 10 mg capsule once daily; do not take more than one 10 mg capsule in 24 hours. A 5 mg product may be appropriate for less severe symptoms.
adults 65 years and over | ask a doctor
children under 6 years of age | ask a doctor
consumers with liver or kidney disease | ask a doctor

Other Information

- store at 20º-25ºC (68º-77ºF)
- avoid high humidity and excessive heat above 40ºC (104ºF)
- protect from light

Inactive ingredients

gelatin, glycerin, mannitol, pharmaceutical ink, polyethylene glycol, purified water, sodium hydroxide, sorbitan, sorbitol

Questions?

call 1-800-910-6874 (Mon-Fri 9AM-5PM EST)

This product is not manufactured or distibuted by the owners of Zyrtec®.

TAMPER EVIDENT: DO NOT USE IF IMPRINTED SAFETY SEAL UNDER CAP IS BROKEN OR MISSING

KEEP THIS CARD FOR COMPLETE WARNINGS AND PRODUCT INFORMATION

Distributed by Target Corporation

Minneapolis, MN 55403

TM & ©2025 Target Brands, Inc.

L0001165

R1025

Principal Display Panel

Compare to active ingredient in Zyrtec®*

Dye-Free

Allergy Relief

Cetirizine HCl capsules, 10 mg

Antihistamine

indoor and outdoor allergies

24 hour relief of sneezing, runny nose, itchy, watery eyes, itchy throat or nose

24 Hours

ACTUAL SIZE

40SOFTGELS**

up & up TM

40 SOFTGELS** (**LIQUID-FILLED CAPSULES)
10 mg EACH